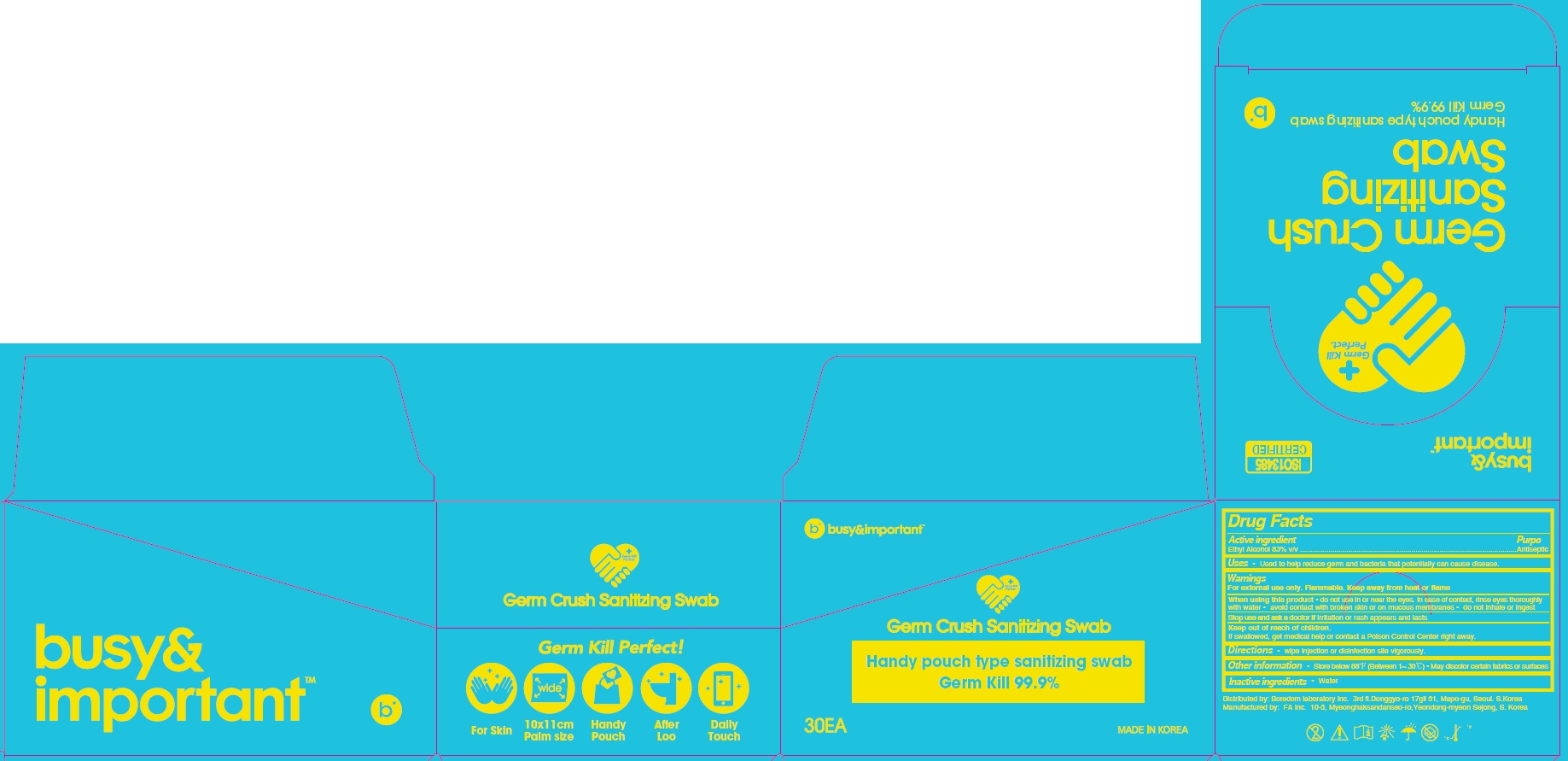 DRUG LABEL: Busy and Important GERM CRUSH SANITIZING
NDC: 74932-350 | Form: SWAB
Manufacturer: FA Inc.
Category: otc | Type: HUMAN OTC DRUG LABEL
Date: 20200909

ACTIVE INGREDIENTS: Alcohol 0.83 1/1 1
INACTIVE INGREDIENTS: Water

ACTIVE INGREDIENT

Ethyl Alcohol 83% v/v

INACTIVE INGREDIENT

Water

PURPOSE

Antiseptic

WARNINGS

For external use only. Flammable. Keep away from heat or flame

--------------------------------------------------------------------------------------------------------
When using this product ■ do not use in or near the eyes. In case of contact, rinse eyes thoroughly with water ■ avoid contact with broken skin or on mucous membranes. ■ do not inhale or ingest
--------------------------------------------------------------------------------------------------------
Stop use and ask a doctor if irritation or rash appears and lasts

KEEP OUT OF REACH OF CHILDREN

If swallowed, get medical help or contact a Poison Control Center right away.

Uses

■ Used to help reduce germ and bacteria that potentially can cause disease.

Directions

■ wipe injection or disinfection site vigorously.

Other Information

■ Store below 86℉(Between 1~30℃)

■ May discolor certain fabrics or surfaces